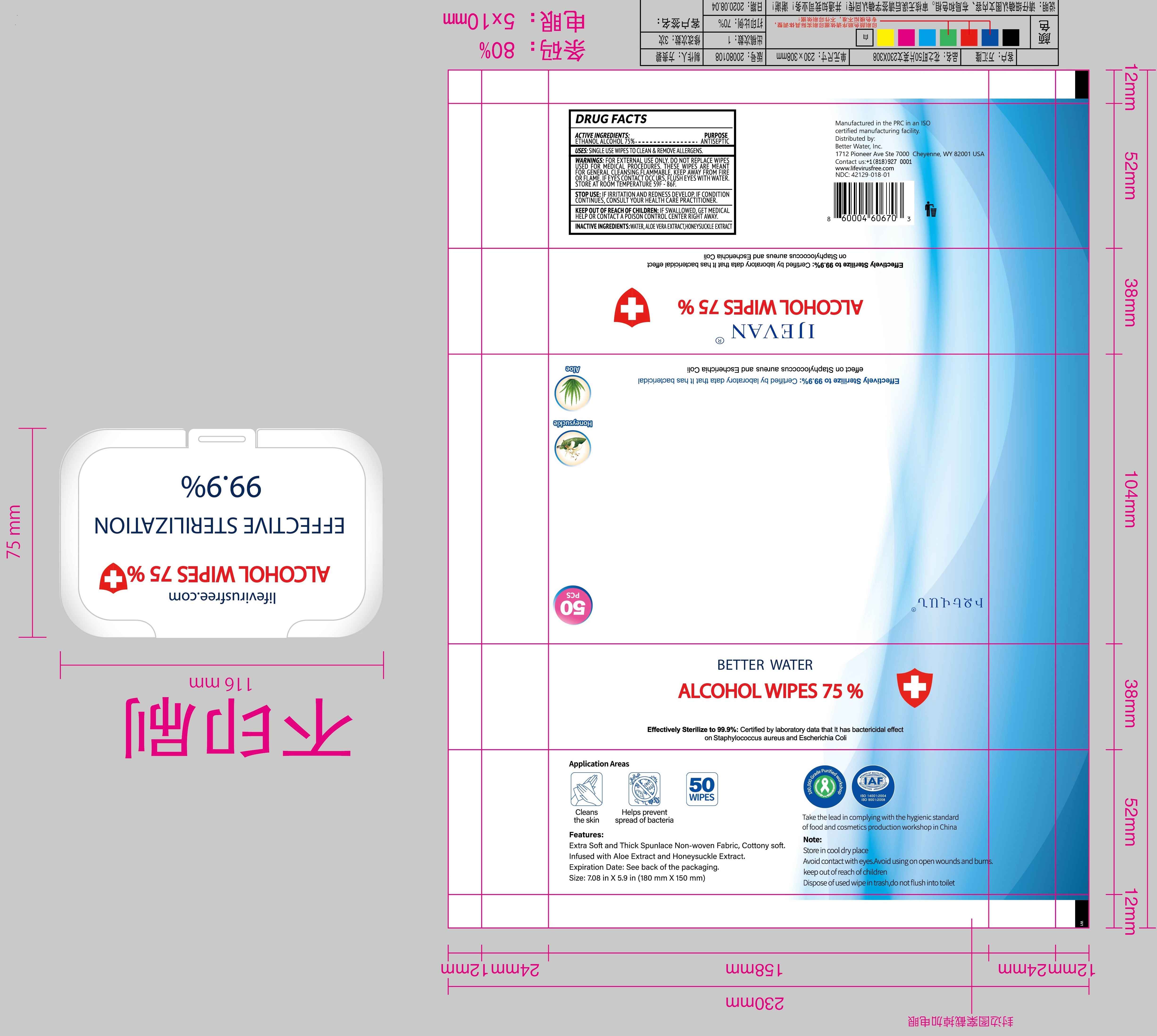 DRUG LABEL: ALCOHOL WIPES 75%
NDC: 42129-018 | Form: CLOTH
Manufacturer: Fustin (Xiamen) Commodity Co., Ltd.
Category: otc | Type: HUMAN OTC DRUG LABEL
Date: 20200828

ACTIVE INGREDIENTS: ALCOHOL 75 g/100 1
INACTIVE INGREDIENTS: LONICERA HYPOGLAUCA WHOLE; WATER; ALOE VERA LEAF

42129-018
ALCOHOL WIPES 75%

Active Ingredient(s)

ETHANOL ALCOHOL 75%

Purpose

Antiseptic

Use

SINGLE USE WIPES TO ClEAN & REMOVEA LLERGENS.

Warnings

FOR EXTERNAL USE ONLY.

DO NOT REPLACE WIIPES USED FOR MEDICAL PROCEDURES. THESE

WIPES ARE MEANT FOR GENERAL CLEANSING.

FLAMMABLE KEEP AWAY FROM FIRE OR FLAME. IF EYES CONTACT

OCCURS, FLUSIH EYES WITH WATER.

STORE AT ROOM TEMPERATURE 59F - 86F.

KEEP OUT OF REACH OF CHILDREN

·Keep out of reach of crildren.lf swallowed get medical help or contact a Poison Control Center right away.

When using this product avoid contact with the eyes. In case of contact, flush eyes thoroughly with water.

Stop use and ask a doctor if irritation and redness develop and persist.

Keep out of reach of children. If swallowed, get medical help or contact a Poison Control Center right away.

Do not use

DO NOT REPLACE WIIPES USED FOR MEDICAL PROCEDURES. THESE

WIPES ARE MEANT FOR GENERAL CLEANSING.

STORAGE AND HANDLING

STORE AT ROOM TEMPERATURE 59F - 86F.

Inactive ingredients

WATER, ALOE VERA EXTRACT,HONEVSUCKLE EXTRACT

DOSAGE AND ADMINISTRATION

FLAMMABLE KEEP AWAY FROM FIRE OR FLAME. IF EYES CONTACT OCCURS, FLUSIH EYES WITH WATER.

STOP USE: IF IRRITATION AND REDNESS DEVELOP. IF C·ONDITl10N CONTINUES, CONSULT YOUR HEALTH CARE PRACTITIONER.